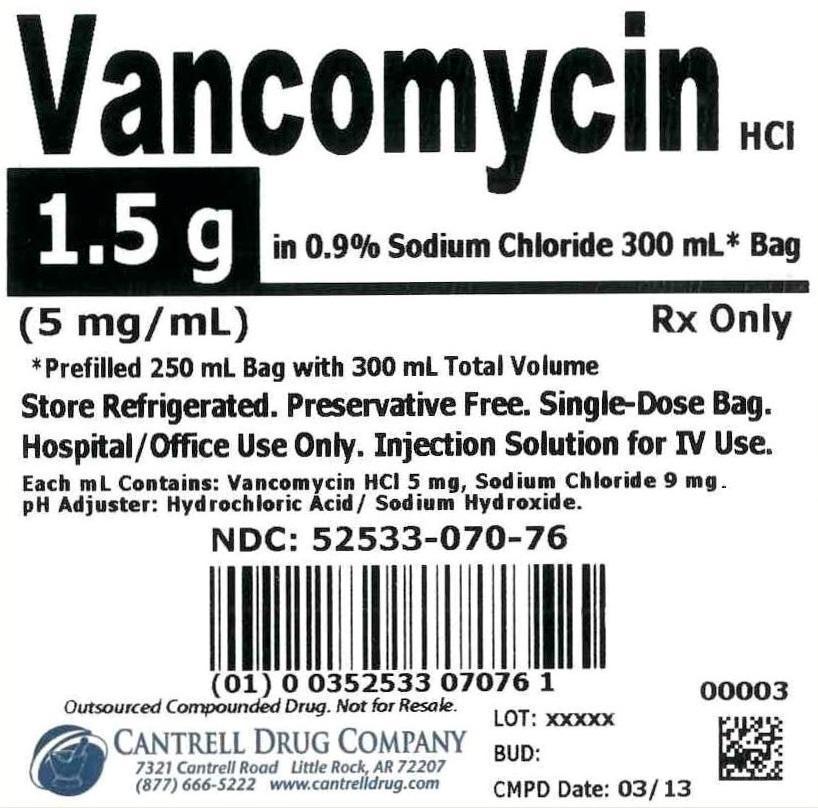 DRUG LABEL: Vancomycin HCl
NDC: 52533-070 | Form: INJECTION, SOLUTION
Manufacturer: Cantrell Drug Company
Category: prescription | Type: HUMAN PRESCRIPTION DRUG LABEL
Date: 20140820

ACTIVE INGREDIENTS: VANCOMYCIN HYDROCHLORIDE 5 mg/1 mL
INACTIVE INGREDIENTS: Sodium Chloride 9 mg/1 mL; Water

Vancomycin HCl 1.5 g in 0.9% Sodium Chloride 300 mL Bag